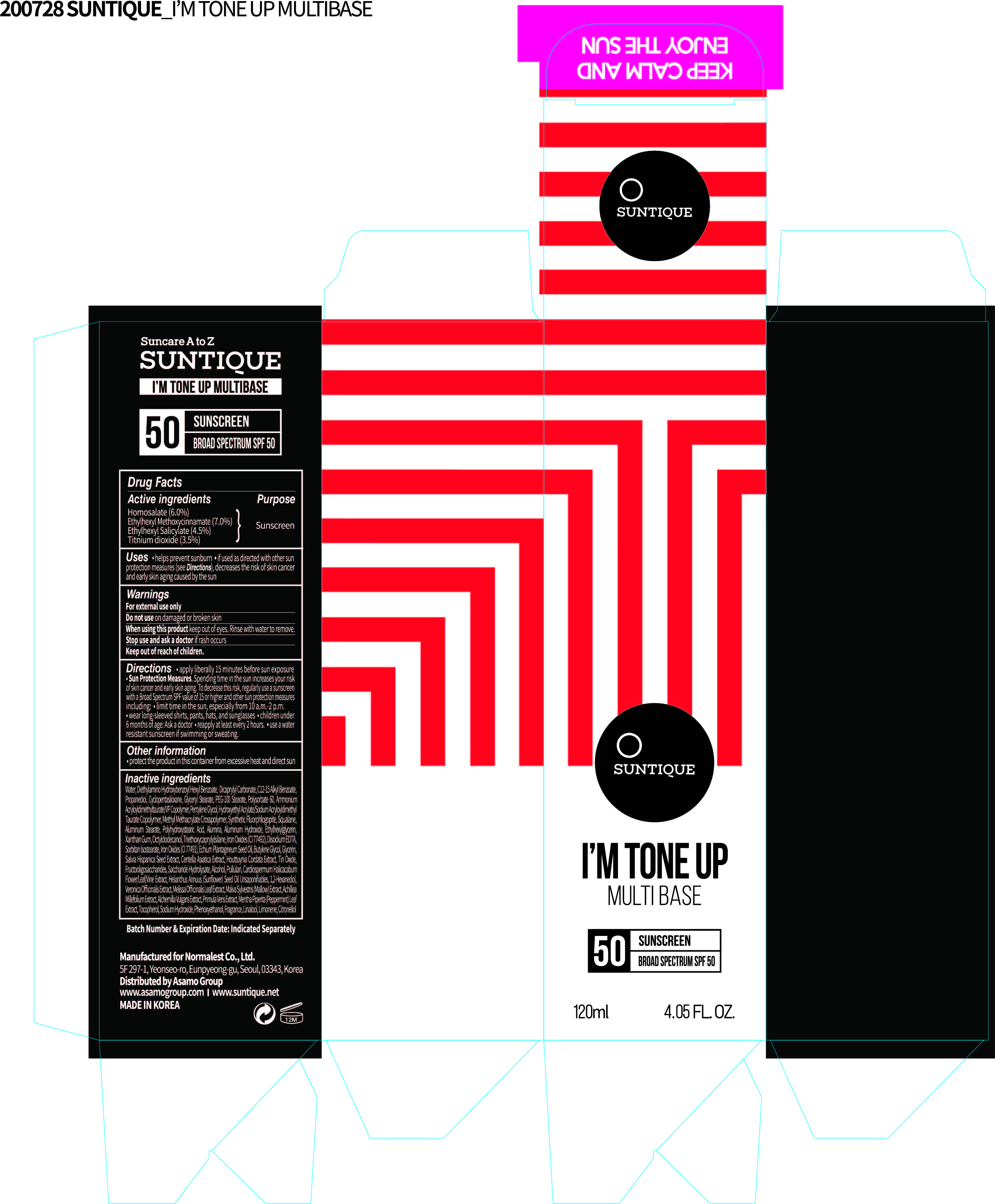 DRUG LABEL: SUNTIQUE IM TONE UP MULTI BASE
NDC: 72284-0012 | Form: LOTION
Manufacturer: Normalest Co., Ltd.
Category: otc | Type: HUMAN OTC DRUG LABEL
Date: 20200728

ACTIVE INGREDIENTS: OCTINOXATE 8.4 g/120 mL; HOMOSALATE 7.2 g/120 mL; OCTISALATE 5.4 g/120 mL; TITANIUM DIOXIDE 4.2 g/120 mL
INACTIVE INGREDIENTS: SQUALANE; FOSFRUCTOSE; INVERT SUGAR; PULLULAN; ALUMINUM OXIDE; ALUMINUM HYDROXIDE; OCTYLDODECANOL; FERRIC OXIDE YELLOW; TRIETHOXYCAPRYLYLSILANE; SORBITAN ISOSTEARATE; FERRIC OXIDE RED; GLYCERIN; STANNIC OXIDE; ACHILLEA MILLEFOLIUM; MELISSA OFFICINALIS LEAF; MENTHA PIPERITA LEAF; TOCOPHEROL; SODIUM HYDROXIDE; WATER; DIETHYLAMINO HYDROXYBENZOYL HEXYL BENZOATE; PROPANEDIOL; ALKYL (C12-15) BENZOATE; CYCLOMETHICONE 5; GLYCERYL MONOSTEARATE; PEG-100 STEARATE; POLYSORBATE 60; SALVIA HISPANICA SEED; CENTELLA ASIATICA; HOUTTUYNIA CORDATA WHOLE; PENTYLENE GLYCOL; HYDROXYETHYL ACRYLATE/SODIUM ACRYLOYLDIMETHYL TAURATE COPOLYMER (100000 MPA.S AT 1.5%); METHYL METHACRYLATE/GLYCOL DIMETHACRYLATE CROSSPOLYMER; PHENOXYETHANOL; DICAPRYLYL CARBONATE; AMMONIUM ACRYLOYLDIMETHYLTAURATE/VP COPOLYMER; 1,2-HEXANEDIOL; ETHYLHEXYLGLYCERIN; XANTHAN GUM; EDETATE DISODIUM; ECHIUM PLANTAGINEUM SEED OIL; BUTYLENE GLYCOL; ALCOHOL; CARDIOSPERMUM HALICACABUM WHOLE; MALVA SYLVESTRIS WHOLE; PRIMULA VERIS; VERONICA OFFICINALIS WHOLE; ALUMINUM STEARATE

SUNTIQUE I'M TONE UP MULTI BASE
120 mL

PACKAGE LABEL

Active ingredients

Octyl Methoxycinnamate 7%

Homosalate 6%

Octyl Salicylate 4.5%

Titanium Dioxide 3.5%

Inactive ingredients

Water, Diethylamino Hydroxybenzoyl Hexyl Benzoate, Dicaprylyl Carbonate, Propanediol, C12-15 Alkyl Benzoate, Cyclopentasiloxane, Glyceryl Stearate, PEG-100 Stearate, Polysorbate 60, Salvia Hispanica Seed Extract, Centella Asiatica Extract, Ammonium Acryloyldimethyltaurate/VP Copolymer, Houttuynia Cordata Extract, Pentylene Glycol, Hydroxyethyl Acrylate/Sodium Acryloyldimethyl Taurate Copolymer, Synthetic Fluorphlogopite, Methyl Methacrylate Crosspolymer, Phenoxyethanol, Squalane, Aluminum Stearate, Fragrance, Fructooligosaccharides, Polyhydroxystearic Acid, Saccharide, Hydrolysate, Pullulan, Alumina, 1,2-Hexanediol, Aluminum Hydroxide, Ethylhexylglycerin, Xanthan Gum, Octyldodecanol, Iron Oxides (CI 77492), Triethoxycaprylylsilane, Disodium EDTA, Sorbitan Isostearate, Iron Oxides (CI 77491), Echium Plantagineum Seed Oil, Butylene Glycol, Glycerin, Tin Oxide, Alcohol, Cardiospermum Halicacabum Flower/Leaf/Vine Extract, Helianthus Annuus (Sunflower) Seed Oil Unsaponifiables, Achillea Millefolium Extract, Alchemilla Vulgaris Extract, Malva Sylvestris (Mallow) Extract ,Melissa Officinalis Leaf Extract, Mentha Piperita (Peppermint) Leaf Extract, Primula Veris Extract, Veronica Officinalis Extract, Tocopherol, Sodium Hydroxide